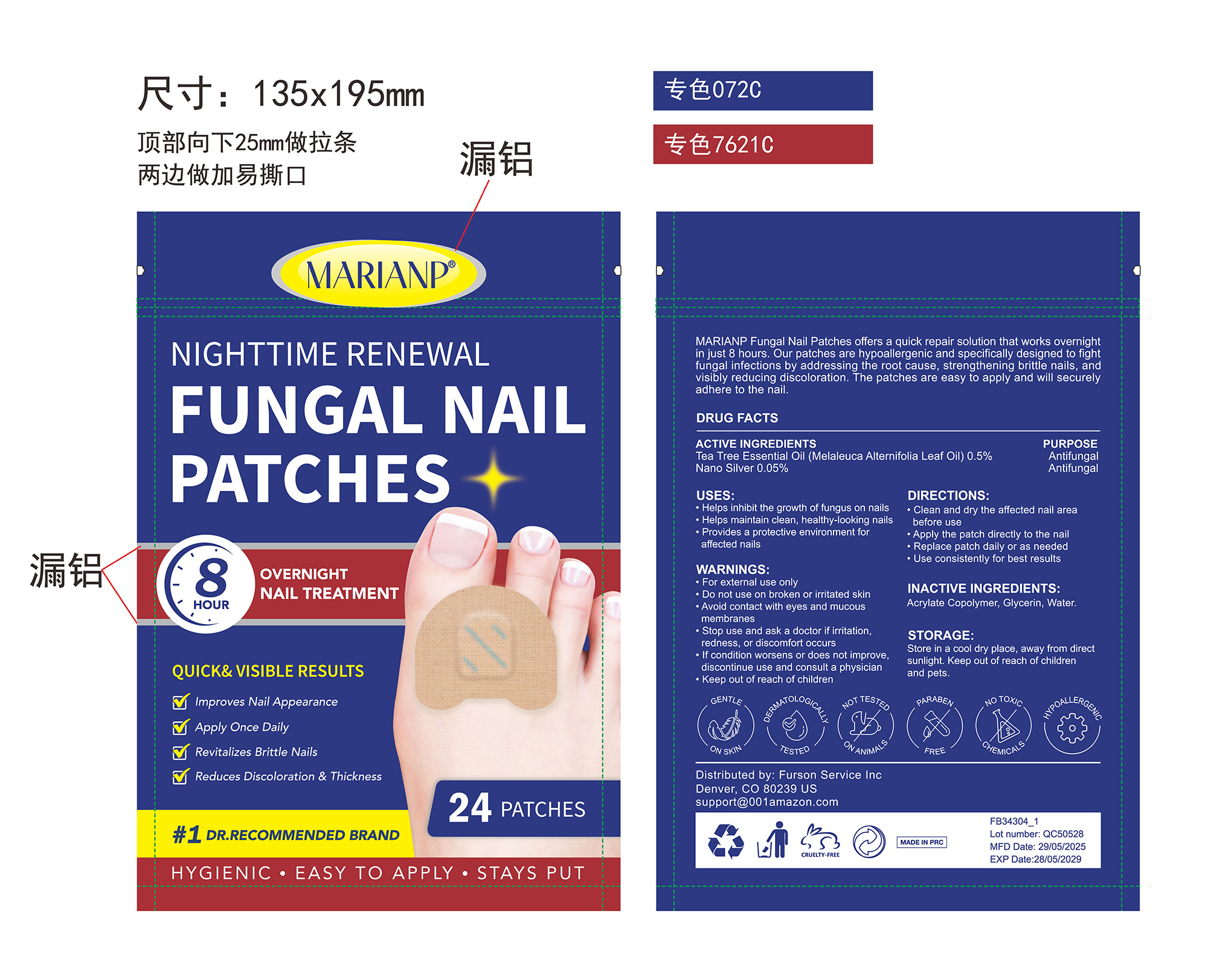 DRUG LABEL: MARIANP FUNGAL NAIL PATCHES
NDC: 83804-015 | Form: PATCH
Manufacturer: Shenzhen Shandian Jingling Technology Co., Ltd.
Category: otc | Type: HUMAN OTC DRUG LABEL
Date: 20260202

ACTIVE INGREDIENTS: TEA TREE OIL 0.005 g/1 1; SILVER 0.0005 g/1 1
INACTIVE INGREDIENTS: WATER; POLYESTER (ADIPIC ACID, 1,6-HEXANEDIOL, NEOPENTYL GLYCOL); GLYCERIN

83804-015 MARIANP FUNGAL NAIL PATCHES

ACTIVE INGREDIENT

TEA TREE OIL 0.5%
Nano Silver 0.05%

PURPOSE

Antifungal

INDICATIONS AND USAGE

Helps inhibit the growth of fungus on nais
Helps maintain clean, healthy-looking nails
Provides a protective environment for affected nails

WARNINGS

For external use only

Do not use on broken or irritated skin

WHEN USING

Avoid contact with eyes and mucous membranes

Stop use and ask a doctor if irritation,redness, or discomfort occurs
If condition worsens or does not improve discontinue use and consult a physician

Keep out of reach of children

DOSAGE AND ADMINISTRATION

Clean and dry the affected nail area before use
Apply the patch directly to the nail
Replace patch daily or as needed
Use consistently for best results

INACTIVE INGREDIENT

Glycerin, Water, Acrylic Copolymer